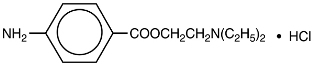 DRUG LABEL: Unknown
Manufacturer: Hospira, Inc.
Category: prescription | Type: Human prescription drug label
Date: 20070828

NOVOCAIN®
PROCAINE HYDROCHLORIDE INJECTION, USP

10% Solution for Spinal Anesthesia

Rx only

DESCRIPTION

NOVOCAIN, procaine hydrochloride, is benzoic acid, 4-amino-, 2-(diethylamino) ethyl ester, monohydrochloride, the ester of diethylaminoethanol and aminobenzoic acid, with the following structural formula:

It is a white crystalline, odorless powder that is freely soluble in water, but less soluble in alcohol. Each mL contains 100 mg procaine hydrochloride and 4 mg acetone sodium bisulfite as antioxidant. DO NOT USE SOLUTIONS IF CRYSTALS, CLOUDINESS, OR DISCOLORATION IS OBSERVED. EXAMINE SOLUTIONS CAREFULLY BEFORE USE. REAUTOCLAVING INCREASES LIKELIHOOD OF CRYSTAL FORMATION.

CLINICAL PHARMACOLOGY

NOVOCAIN stabilizes the neuronal membrane and prevents the initiation and transmission of nerve impulses, thereby effecting local anesthesia. NOVOCAIN lacks surface anesthetic activity. The onset of action is rapid (2 to 5 minutes) and the duration of action is relatively short (average 1 to 1½ hours), depending upon the anesthetic technique, the type of block, the concentration, and the individual patient.

NOVOCAIN is readily absorbed following parenteral administration and is rapidly hydrolyzed by plasma cholinesterase to aminobenzoic acid and diethylaminoethanol.

A vasoconstrictor may be added to the solution of NOVOCAIN to promote local hemostasis, delay systemic absorption, and increase duration of anesthesia.

INDICATIONS AND USAGE

NOVOCAIN is indicated for spinal anesthesia.

CONTRAINDICATIONS

Spinal anesthesia with NOVOCAIN is contraindicated in patients with generalized septicemia: sepsis at the proposed injection site; certain diseases of the cerebrospinal system, e.g., meningitis, syphilis; and a known hypersensitivity to the drug, drugs of a similar chemical configuration, or aminobenzoic acid or its derivatives.

The decision as to whether or not spinal anesthesia should be used in an individual case should be made by the physician after weighing the advantages with the risks and possible complications.

WARNINGS

RESUSCITATIVE EQUIPMENT AND DRUGS SHOULD BE IMMEDIATELY AVAILABLE WHENEVER ANY LOCAL ANESTHETIC DRUG IS USED. Spinal anesthesia should only be administered by those qualified to do so.

Large doses of local anesthetics should not be used in patients with heartblock.

Reactions resulting in fatality have occurred on rare occasions with the use of local anesthetics, even in the absence of a history of hypersensitivity.

Usage in Pregnancy. Safe use of NOVOCAIN has not been established with respect to adverse effects on fetal development. Careful consideration should be given to this fact before administering this drug to women of childbearing potential particularly during early pregnancy. This does not exclude the use of the drug at term for obstetrical analgesia. Vasopressor agents (administered for the treatment of hypotension or added to the anesthetic solution for vasoconstriction) should be used with extreme caution in the presence of oxytocic drugs as they may produce severe, persistent hypertension with possible rupture of a cerebral blood vessel.

Solutions which contain a vasoconstrictor should be used with extreme caution in patients receiving drugs known to produce alterations in blood pressure (i.e., monoamine oxidase inhibitors (MAOI), tricyclic antidepressants, phenothiazines, etc.), as either severe sustained hypertension or hypotension may occur.

Local anesthetic procedures should be used with caution when there is inflammation and/or sepsis in the region of the proposed injection.

Contains acetone sodium bisulfite, a sulfite that may cause allergic-type reactions including anaphylactic symptoms and life-threatening or less severe asthmatic episodes in certain susceptible people. The overall prevalence of sulfite sensitivity in the general population is unknown and probably low. Sulfite sensitivity is seen more frequently in asthmatic than in nonasthmatic people.

PRECAUTIONS

Standard textbooks should be consulted for specific techniques and precautions for various spinal anesthetic procedures.

The safety and effectiveness of a spinal anesthetic depend upon proper dosage, correct technique, adequate precautions, and readiness for emergencies. The lowest dosage that results in effective anesthesia should be used to avoid high plasma levels and possible adverse effects. Tolerance varies with the status of the patient. Debilitated, elderly patients, or acutely ill patients should be given reduced doses commensurate with their weight and physical status. Reduced dosages are also indicated for obstetric delivery and patients with increased intra-abdominal pressure.

The decision whether or not to use spinal anesthesia in the following disease states depends on the physician’s appraisal of the advantages as opposed to the risk: cardiovascular disease (i.e., shock, hypertension, anemia, etc.), pulmonary disease, renal impairment, metabolic or endocrine disorders, gastrointestinal disorders (i.e., intestinal obstruction, peritonitis, etc.), or complicated obstetrical deliveries.

NOVOCAIN SHOULD BE USED WITH CAUTION IN PATIENTS WITH KNOWN DRUG ALLERGIES AND SENSITIVITIES. A thorough history of the patient’s prior experience with NOVOCAIN or other local anesthetics as well as concomitant or recent drug use should be taken (see CONTRAINDICATIONS). NOVOCAIN should not be used in any condition in which a sulfonamide drug is being employed since aminobenzoic acid inhibits the action of sulfonamides.

Solutions containing a vasopressor should be used with caution in the presence of diseases which may adversely affect the cardiovascular system.

NOVOCAIN should be used with caution in patients with severe disturbances of cardiac rhythm, shock or heartblock.

ADVERSE REACTIONS

Systemic adverse reactions involving the central nervous system and the cardiovascular system usually result from high plasma levels due to excessive dosage, rapid absorption, or inadvertent intravascular injection. In addition, use of inappropriate doses or techniques may result in extensive spinal blockade leading to hypotension and respiratory arrest.

A small number of reactions may result from hypersensitivity, idiosyncrasy, or diminished tolerance to normal dosage.

Excitatory CNS effects (nervousness, dizziness, blurred vision, tremors) commonly represent the initial signs of local anesthetic systemic toxicity. However, these reactions may be very brief or absent in some patients in which case the first manifestation of toxicity may be drowsiness or convulsions merging into unconsciousness and respiratory arrest.

Cardiovascular system reactions include depression of the myocardium, hypotension (or sometimes hypertension), bradycardia, and even cardiac arrest.

Allergic reactions are characterized by cutaneous lesions of delayed onset, or urticaria, edema, and other manifestations of allergy. The detection of sensitivity by skin testing is of limited value. As with other local anesthetics, hypersensitivity, idiosyncrasy and anaphylactoid reactions have occurred rarely. The reaction may be abrupt and severe and is not usually dose related.

The following adverse reactions may occur with spinal anesthesia: Central Nervous System: postspinal headache, meningismus, arachnoiditis, palsies, or spinal nerve paralysis. Cardiovascular: hypotension due to vasomotor paralysis and pooling of the blood in the venous bed. Respiratory: respiratory impairment or paralysis due to the level of anesthesia extending to the upper thoracic and cervical segments. Gastrointestinal: nausea and vomiting.

Treatment of Reactions. Toxic effects of local anesthetics require symptomatic treatment: there is no specific cure. The physician should be prepared to maintain an airway and to support ventilation with oxygen and assisted or controlled respiration as required. Supportive treatment of the cardiovascular system includes intravenous fluids and, when appropriate, vasopressors (preferably those that stimulate the myocardium, such as ephedrine). Convulsions may be controlled with oxygen and by the intravenous administration of diazepam or ultrashort-acting barbiturates or a short-acting muscle relaxant (succinylcholine). Intravenous anticonvulsant agents and muscle relaxants should only be administered by those familiar with their use and only when ventilation and oxygenation are assured. In spinal and epidural anesthesia, sympathetic blockade also occurs as a pharmacological reaction, resulting in peripheral vasodilation and often hypotension. The extent of the hypotension will usually depend on the number of dermatomes blocked. The blood pressure should therefore be monitored in the early phases of anesthesia. If hypotension occurs, it is readily controlled by vasoconstrictors administered either by the intramuscular or the intravenous route, the dosage of which would depend on the severity of the hypotension and the response to treatment.

DOSAGE AND ADMINISTRATION

As with all local anesthetics, the dose of NOVOCAIN varies and depends upon the area to be anesthetized, the vascularity of the tissues, the number of neuronal segments to be blocked, individual tolerance, and the technique of anesthesia. The lowest dose needed to provide effective anesthesia should be administered. For specific techniques and procedures, refer to standard textbooks.

RECOMMENDED DOSAGE FOR SPINAL ANESTHESIA
Extent of Anesthesia | NOVOCAIN; 10% Solution |  | Total Dose; (mg) | Site of Injection; (lumbar interspace)
Extent of Anesthesia | Volume of 10% Solution; (mL) | Volume of Dilution; (mL) | Total Dose; (mg) | Site of Injection; (lumbar interspace)
Perineum | 0.5 | 0.5 | 50 | 4th
Perineum and lower; extremities | 1 | 1 | 100 | 3rd or 4th
Up to costal margin | 2 | 1 | 200 | 2nd, 3rd or 4th

The diluent may be sterile normal saline, sterile distilled water, spinal fluid; and for hyperbaric technique, sterile dextrose solution.

The usual rate of injection is 1 mL per 5 seconds. Full anesthesia and fixation usually occur in 5 minutes.

STERILIZATION

The drug in intact ampuls is sterile. The preferred method of destroying bacteria on the exterior of ampuls before opening is heat sterilization (autoclaving). Immersion in antiseptic solution is not recommended.

Autoclave at 15-pound pressure, at 121°C (250°F), for 15 minutes. The diluent dextrose may show some brown discoloration due to caramelization.

Protect solutions from light.

HOW SUPPLIED

List | Container | Concentration | Fill | Quantity
1810 | Uni-Amp® Unit Dose Pak | 10% | 2 mL | 25
1810 | Single-Dose Ampuls | 10% | 2 mL | 25

Store at 20 to 25°C (68 to 77°F). [See USP Controlled Room Temperature.]

Revised: July, 2005

©Hospira 2005 | EN-1078 | Printed in USA

Hospira, Inc., Lake Forest, IL 60045 USA